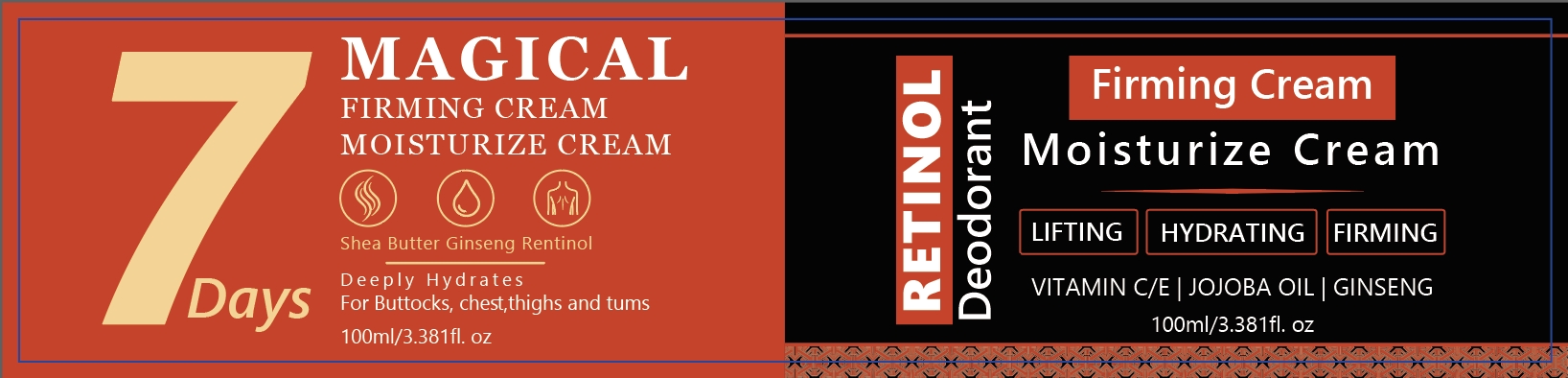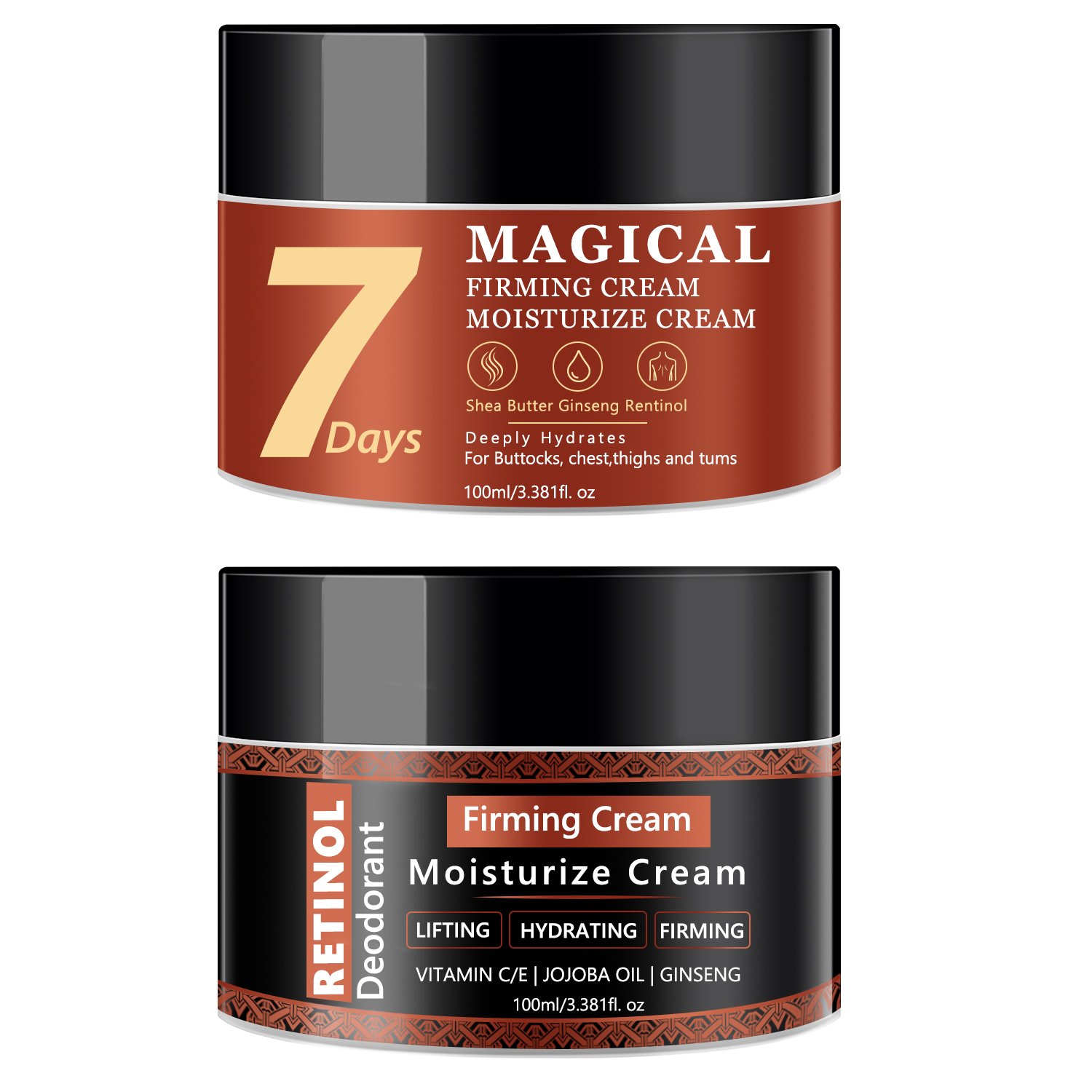 DRUG LABEL: Moisturize Cream
NDC: 84025-228 | Form: CREAM
Manufacturer: Guangzhou Yanxi Biotechnology Co., Ltd
Category: otc | Type: HUMAN OTC DRUG LABEL
Date: 20241021

ACTIVE INGREDIENTS: SIMMONDSIA CHINENSIS (JOJOBA) SEED OIL 3 mg/100 mL; ALOE BARBADENSIS LEAF EXTRACT 5 mg/100 mL
INACTIVE INGREDIENTS: WATER

DOSAGE AND ADMINISTRATION

To use, smooth this body moisturizer for dry skin over body daily

WARNINGS

keep out of children

INACTIVE INGREDIENT

Aqua

INDICATIONS AND USAGE

for daily body care

keep out of chilidren

PURPOSE

cream for all-over hydration, wherever you need it